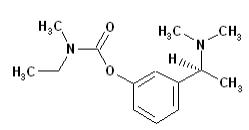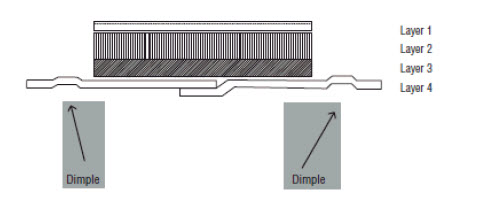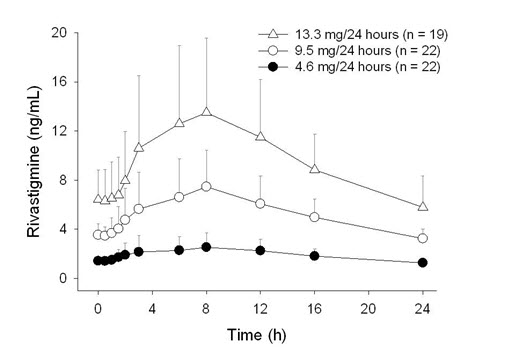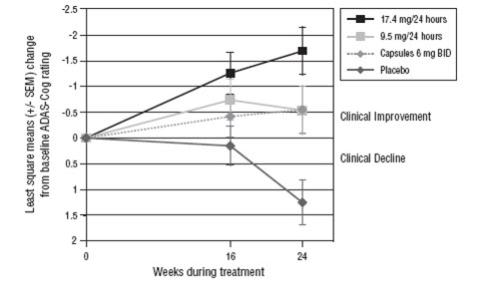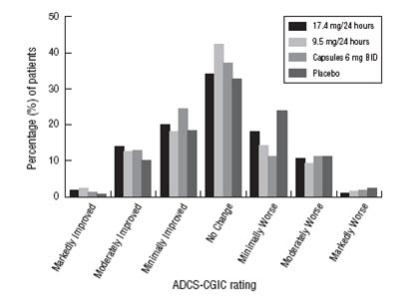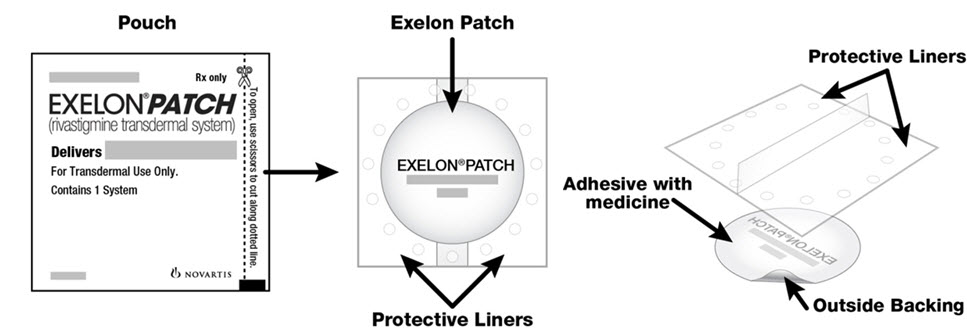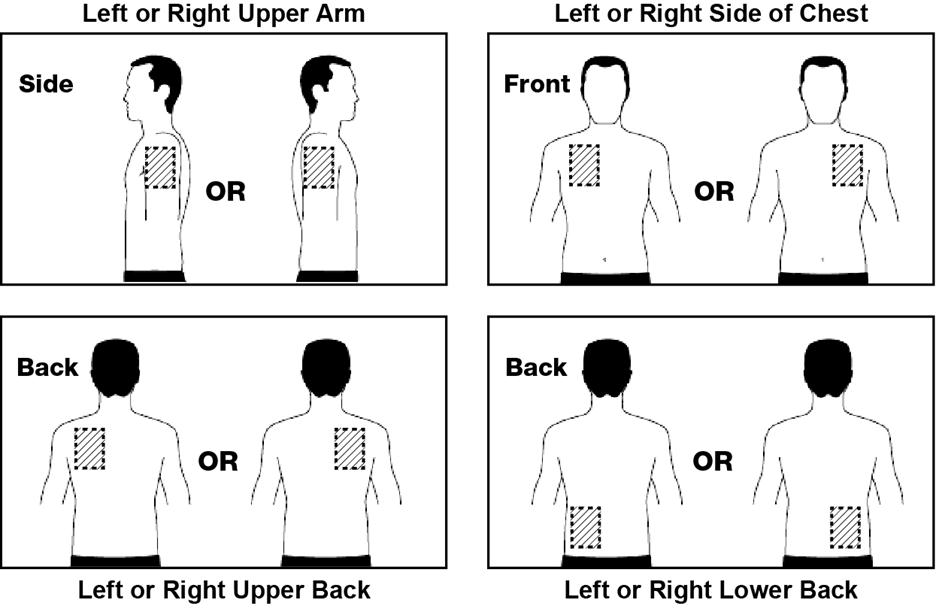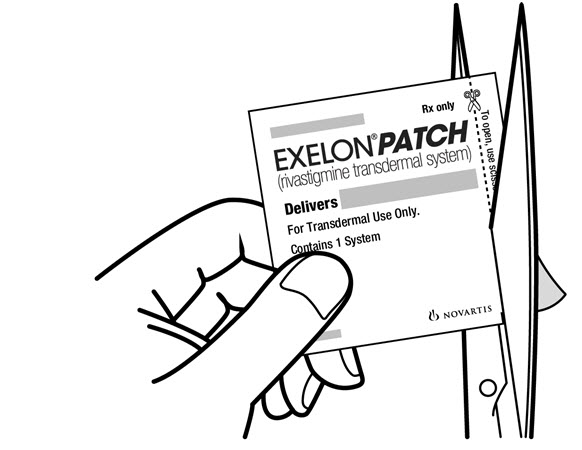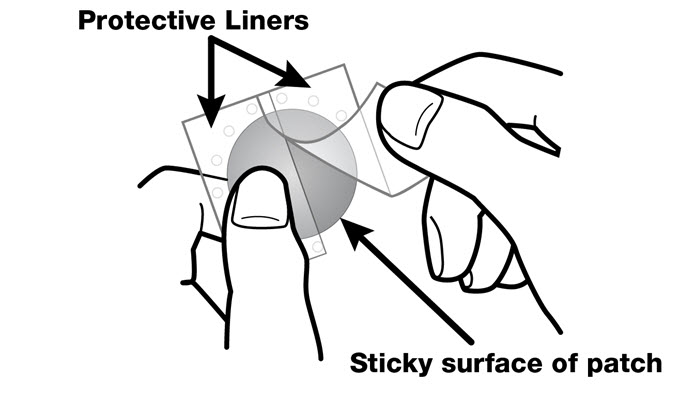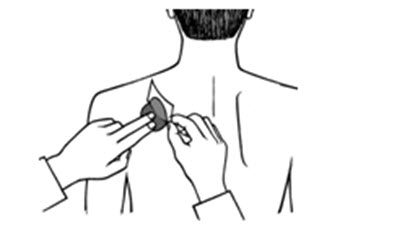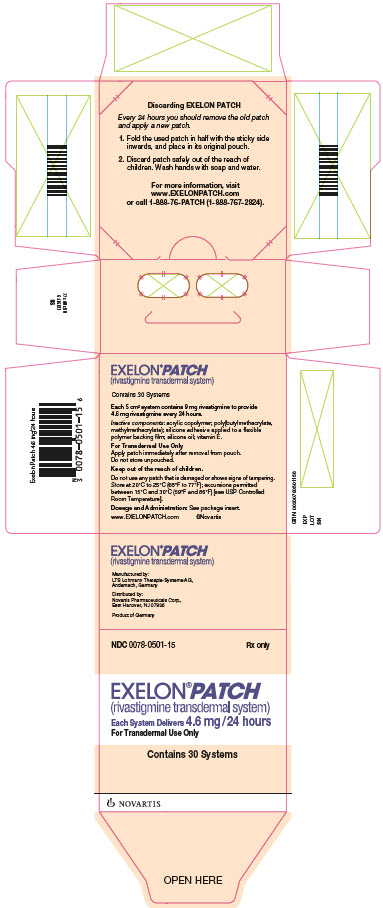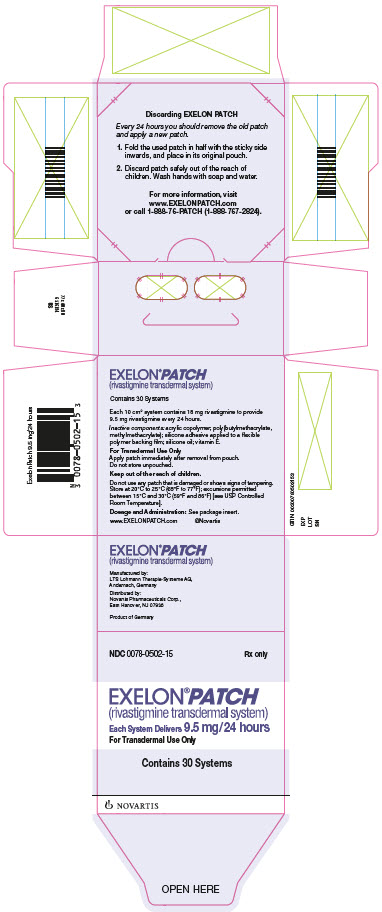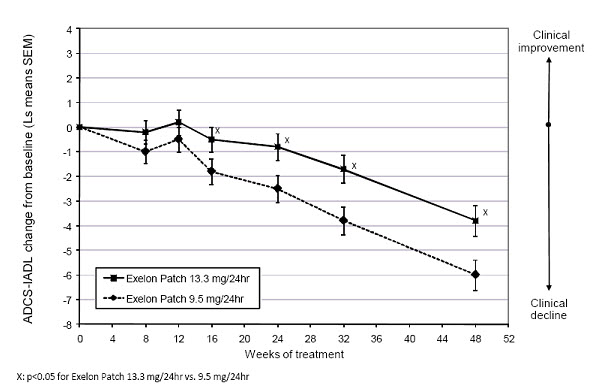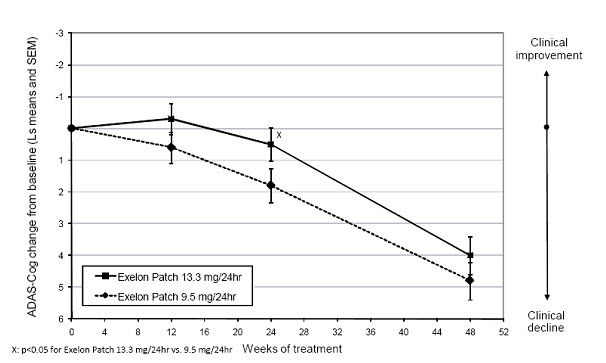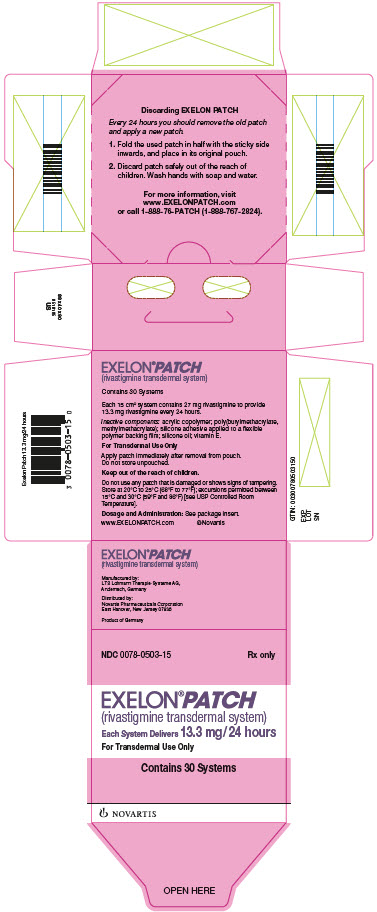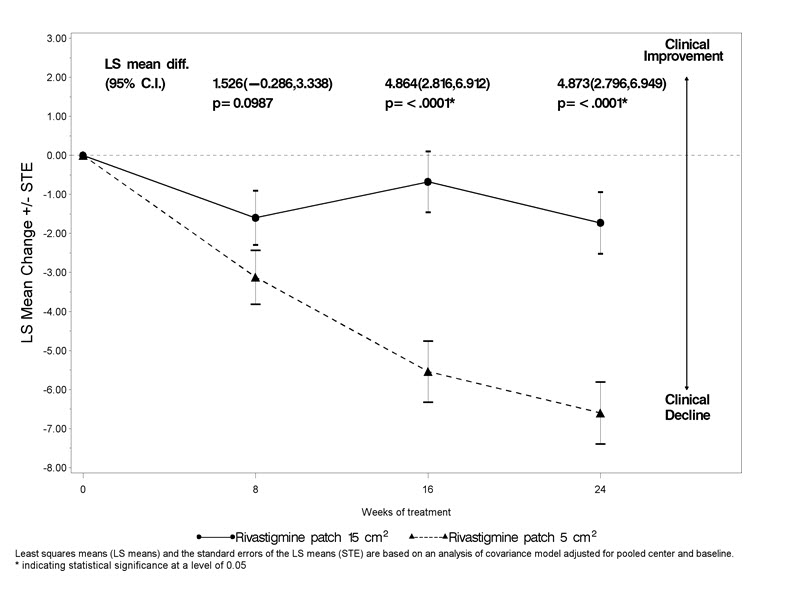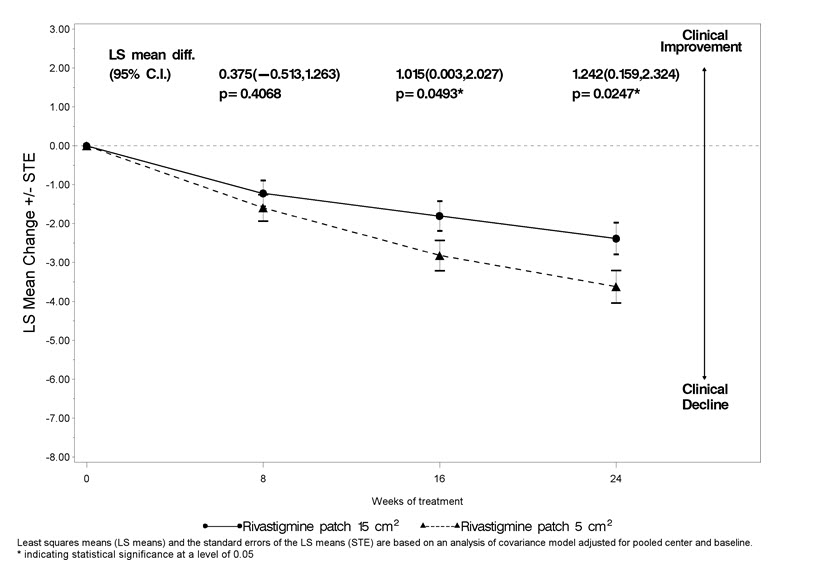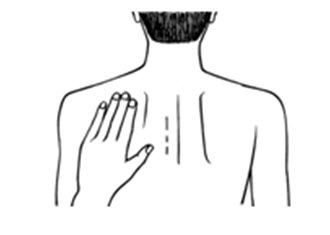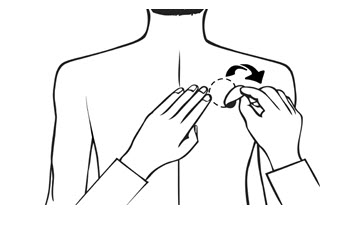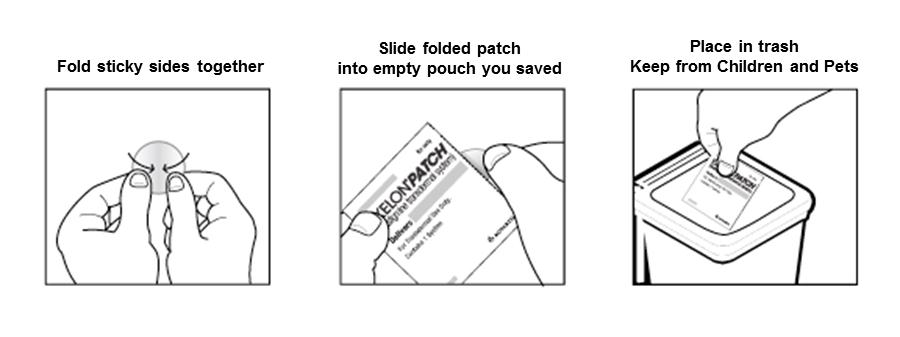 DRUG LABEL: Exelon
NDC: 0078-0501 | Form: PATCH, EXTENDED RELEASE
Manufacturer: Novartis Pharmaceuticals Corporation
Category: prescription | Type: HUMAN PRESCRIPTION DRUG LABEL
Date: 20240508

ACTIVE INGREDIENTS: RIVASTIGMINE 4.6 mg/24 h
INACTIVE INGREDIENTS: .ALPHA.-TOCOPHEROL

HIGHLIGHTS OF PRESCRIBING INFORMATION

These highlights do not include all the information needed to use EXELON PATCH safely and effectively. See full prescribing information for EXELON PATCH.
EXELON® PATCH (rivastigmine transdermal system)
Initial U.S. Approval: 2000

1 INDICATIONS AND USAGE

EXELON PATCH is an acetylcholinesterase inhibitor indicated for treatment of:

- Mild, moderate, and severe dementia of the Alzheimer’s type (AD). (1.1)
- Mild-to-moderate dementia associated with Parkinson’s disease (PD). (1.2)

2 DOSAGE AND ADMINISTRATION

- Apply patch on intact skin for a 24-hour period; replace with a new patch every 24 hours. (2.1, 2.4)
- Initial Dose: Initiate treatment with 4.6 mg/24 hours EXELON PATCH. (2.1)
- Dose Titration:
  After a minimum of 4 weeks, if tolerated, increase dose to 9.5 mg/24 hours, which is the minimum effective dose. Following a minimum additional 4 weeks, may increase dosage to maximum dosage of 13.3 mg/24 hours. (2.1)
- Mild-to-Moderate Alzheimer’s Disease and Parkinson’s Disease Dementia: EXELON PATCH 9.5 mg/24 hours or 13.3 mg/24 hours once daily. (2.1)
- Severe Alzheimer’s Disease: EXELON PATCH 13.3 mg/24 hours once daily. (2.1)
- For treatment interruption longer than 3 days, retitrate dosage starting at 4.6 mg per 24 hours. (2.1)
- Consider dose adjustments in patients with (2.2):
  - Mild-to-moderate hepatic impairment (8.6)
  - Low (less than 50 kg) body weight (8.7)

3 DOSAGE FORMS AND STRENGTHS

Patch: 4.6 mg/24 hours or 9.5 mg/24 hours or 13.3 mg/24 hours (3)

4 CONTRAINDICATIONS

- Known hypersensitivity to rivastigmine, other carbamate derivatives, or other components of the formulation. (4)
- History of application-site reactions with rivastigmine transdermal patch suggestive of allergic contact dermatitis. (4, 6.2)

5 WARNINGS AND PRECAUTIONS

- Hospitalization and, rarely, death have been reported due to application of multiple patches at same time. Ensure patients or caregivers receive instruction on proper dosing and administration. (5.1)
- Gastrointestinal Adverse Reactions: May include significant nausea, vomiting, diarrhea, anorexia/decreased appetite, and weight loss, and may necessitate treatment interruption. Dehydration may result from prolonged vomiting or diarrhea and can be associated with serious outcomes. (5.2)
- Application-site reactions may occur with the patch form of rivastigmine. Discontinue treatment if application-site reactions spread beyond the patch size, if there is evidence of a more intense local reaction (e.g., increasing erythema, edema, papules, vesicles), and if symptoms do not significantly improve within 48 hours after patch removal. (5.3)

6 ADVERSE REACTIONS

Most common adverse reactions (less than 5% and higher than with placebo): Nausea, vomiting, and diarrhea. (6.1)

To report SUSPECTED ADVERSE REACTIONS, contact Novartis Pharmaceuticals Corporation at 1-888-669-6682 or FDA at 1-800-FDA-1088 or www.fda.gov/medwatch.

7 DRUG INTERACTIONS

Concomitant use with metoclopramide, beta-blockers, or cholinomimetics and anticholinergic medications is not recommended. (7.1, 7.2, 7.3)

FULL PRESCRIBING INFORMATION

1 INDICATIONS AND USAGE

1.1 Alzheimer’s Disease

EXELON PATCH is indicated for the treatment of dementia of the Alzheimer’s type (AD). Efficacy has been demonstrated in patients with mild, moderate, and severe Alzheimer’s disease.

1.2 Parkinson’s Disease Dementia

EXELON PATCH is indicated for the treatment of mild-to-moderate dementia associated with Parkinson’s disease (PDD).

2 DOSAGE AND ADMINISTRATION

2.1 Recommended Dosing

Initial Dose

Initiate treatment with one 4.6 mg/24 hours EXELON PATCH applied to the skin once daily [see Dosage and Administration (2.4)].

Dose Titration

Increase the dose only after a minimum of 4 weeks at the previous dose, and only if the previous dose has been tolerated. For mild-to-moderate AD and PDD patients, continue the effective dose of 9.5 mg/24 hours for as long as therapeutic benefit persists. Patients can then be increased to the maximum effective dose of 13.3 mg/24 hours dose. For patients with severe AD, 13.3 mg/24 hours is the effective dose. Doses higher than 13.3 mg/24 hours confer no appreciable additional benefit, and are associated with an increase in the incidence of adverse reactions [see Warnings and Precautions (5.2), Adverse Reactions (6.1)].

Mild-to-Moderate Alzheimer’s Disease and Mild-to-Moderate Parkinson’s Disease Dementia

The effective dosage of EXELON PATCH is 9.5 mg/24 hours or 13.3 mg/24 hours administered once per day; replace with a new patch every 24 hours.

Severe Alzheimer’s Disease

The effective dosage of EXELON PATCH in patients with severe Alzheimer’s disease is 13.3 mg/24 hours administered once per day; replace with a new patch every 24 hours.

Interruption of Treatment

If dosing is interrupted for 3 days or fewer, restart treatment with the same or lower strength EXELON PATCH. If dosing is interrupted for more than 3 days, restart treatment with the 4.6 mg/24 hours EXELON PATCH and titrate as described above.

2.2 Dosing in Specific Populations

Dosing Modifications in Patients with Hepatic Impairment

Consider using the 4.6 mg/24 hours EXELON PATCH as both the initial and maintenance dose in patients with mild (Child-Pugh score 5 to 6) to moderate (Child-Pugh score 7 to 9) hepatic impairment [see Use in Specific Populations (8.6), Clinical Pharmacology (12.3)].

Dosing Modifications in Patients with Low Body Weight

Carefully titrate and monitor patients with low body weight (less than 50 kg) for toxicities (e.g., excessive nausea, vomiting), and consider reducing the maintenance dose to the 4.6 mg/24 hours EXELON PATCH if such toxicities develop.

2.3 Switching to EXELON PATCH from EXELON Capsules or EXELON Oral Solution

Patients treated with EXELON Capsules or Oral Solution may be switched to EXELON PATCH as follows:

- A patient who is on a total daily dose of less than 6 mg of oral rivastigmine can be switched to the 4.6 mg/24 hours EXELON PATCH.
- A patient who is on a total daily dose of 6 mg to 12 mg of oral rivastigmine can be switched to the 9.5 mg/24 hours EXELON PATCH.

Instruct patients or caregivers to apply the first patch on the day following the last oral dose.

2.4 Important Administration Instructions

EXELON PATCH is for transdermal use on intact skin.

(a) Do not use the patch if the pouch seal is broken or the patch is cut, damaged, or changed in any way.

(b) Apply the EXELON PATCH once a day.

- Press down firmly for 30 seconds until the edges stick well when applying to clean, dry, hairless, intact healthy skin in a place that will not be rubbed against by tight clothing.
- Use the upper or lower back as the site of application because the patch is less likely to be removed by the patient. If sites on the back are not accessible, apply the patch to the upper arm or chest.
- Do not apply to a skin area where cream, lotion, or powder has recently been applied.

(c) Do not apply to skin that is red, irritated, or cut.

(d) Replace the EXELON PATCH with a new patch every 24 hours. Instruct patients to only wear 1 patch at a time (remove the previous day’s patch before applying a new patch) [see Warnings and Precautions (5.1), Overdosage (10)]. If a patch falls off or if a dose is missed, apply a new patch immediately, and then replace this patch the following day at the usual application time.

(e) Change the site of patch application daily to minimize potential irritation, although a new patch can be applied to the same general anatomic site (e.g., another spot on the upper back) on consecutive days. Do not apply a new patch to the same location for at least 14 days.

(f) May wear the patch during bathing and in hot weather. Avoid long exposure to external heat sources (excessive sunlight, saunas, solariums).

(g) Place used patches in the previously saved pouch and discard in the trash, away from pets or children.

(h) Wash hands with soap and water after removing the patch. In case of contact with eyes or if the eyes become red after handling the patch, rinse immediately with plenty of water, and seek medical advice if symptoms do not resolve.

3 DOSAGE FORMS AND STRENGTHS

EXELON PATCH is available in 3 strengths. Each patch has a beige backing layer labeled as either:

- EXELON® PATCH 4.6 mg/24 hours, AMCX
- EXELON® PATCH 9.5 mg/24 hours, BHDI
- EXELON® PATCH 13.3 mg/24 hours, CNFU

4 CONTRAINDICATIONS

EXELON PATCH is contraindicated in patients with:

- known hypersensitivity to rivastigmine, other carbamate derivatives, or other components of the formulation [see Description (11)]
- previous history of application-site reactions with rivastigmine transdermal patch suggestive of allergic contact dermatitis [see Warnings and Precautions (5.3)].

Isolated cases of generalized skin reactions have been described in postmarketing experience [see Adverse Reactions (6.2)].

5 WARNINGS AND PRECAUTIONS

5.1 Medication Errors Resulting in Overdose

Medication errors with EXELON PATCH have resulted in serious adverse reactions; some cases have required hospitalization, and rarely, led to death. The majority of medication errors have involved not removing the old patch when putting on a new one and the use of multiple patches at one time.

Instruct patients and their caregivers on important administration instructions for EXELON PATCH [see Dosage and Administration (2.4)].

5.2 Gastrointestinal Adverse Reactions

EXELON PATCH can cause gastrointestinal adverse reactions, including significant nausea, vomiting, diarrhea, anorexia/decreased appetite, and weight loss. Dehydration may result from prolonged vomiting or diarrhea and can be associated with serious outcomes. The incidence and severity of these reactions are dose-related [see Adverse Reactions (6.1)]. For this reason, initiate treatment with EXELON PATCH at a dose of 4.6 mg/24 hours, and titrate to a dose of 9.5 mg/24 hours and then to a dose of 13.3 mg/24 hours, if appropriate [see Dosage and Administration (2.1)].

If treatment is interrupted for more than 3 days because of intolerance, reinitiate EXELON PATCH with the 4.6 mg/24 hours dose to reduce the possibility of severe vomiting and its potentially serious sequelae. A postmarketing report described a case of severe vomiting with esophageal rupture following inappropriate reinitiation of treatment of an oral formulation of rivastigmine without retitration after 8 weeks of treatment interruption.

Inform caregivers to monitor for gastrointestinal adverse reactions and to inform the physician if they occur. It is critical to inform caregivers that if therapy has been interrupted for more than 3 days because of intolerance, the next dose should not be administered without contacting the physician regarding proper retitration.

5.3 Skin Reactions

Skin application-site reactions may occur with EXELON PATCH. These reactions are not in themselves an indication of sensitization. However, use of rivastigmine patch may lead to allergic contact dermatitis.

Allergic contact dermatitis should be suspected if application-site reactions spread beyond the patch size, if there is evidence of a more intense local reaction (e.g., increasing erythema, edema, papules, vesicles), and if symptoms do not significantly improve within 48 hours after patch removal. In these cases, treatment should be discontinued [see Contraindications (4)].

In patients who develop application-site reactions to EXELON PATCH, suggestive of allergic contact dermatitis and who still require rivastigmine, treatment should be switched to oral rivastigmine only after negative allergy testing and under close medical supervision. It is possible that some patients sensitized to rivastigmine by exposure to rivastigmine patch may not be able to take rivastigmine in any form.

There have been isolated postmarketing reports of patients experiencing disseminated allergic dermatitis when administered rivastigmine irrespective of the route of administration (oral or transdermal). In these cases, treatment should be discontinued [see Contraindications (4)]. Patients and caregivers should be instructed accordingly.

5.4 Other Adverse Reactions From Increased Cholinergic Activity

Neurologic Effects

Extrapyramidal Symptoms: Cholinomimetics, including rivastigmine, may exacerbate or induce extrapyramidal symptoms. Worsening of parkinsonian symptoms, particularly tremor, has been observed in patients with dementia associated with Parkinson’s disease who were treated with EXELON Capsules.

Seizures: Drugs that increase cholinergic activity are believed to have some potential for causing seizures. However, seizure activity also may be a manifestation of Alzheimer's disease.

Peptic Ulcers/Gastrointestinal Bleeding

Cholinesterase inhibitors, including rivastigmine, may increase gastric acid secretion due to increased cholinergic activity. Monitor patients using EXELON PATCH for symptoms of active or occult gastrointestinal bleeding, especially those at increased risk for developing ulcers, e.g., those with a history of ulcer disease or those receiving concurrent nonsteroidal anti-inflammatory drugs (NSAIDs). Clinical studies of rivastigmine have shown no significant increase, relative to placebo, in the incidence of either peptic ulcer disease or gastrointestinal bleeding.

Use with Anesthesia

Rivastigmine, as a cholinesterase inhibitor, is likely to exaggerate succinylcholine-type muscle relaxation during anesthesia.

Cardiac Conduction Effects

Because rivastigmine increases cholinergic activity, use of the EXELON PATCH may have vagotonic effects on heart rate (e.g., bradycardia). The potential for this action may be particularly important in patients with sick sinus syndrome or other supraventricular cardiac conduction conditions.

Genitourinary Effects

Although not observed in clinical trials of rivastigmine, drugs that increase cholinergic activity may cause urinary obstruction.

Pulmonary Effects

Drugs that increase cholinergic activity, including EXELON PATCH, should be used with care in patients with a history of asthma or obstructive pulmonary disease.

5.5 Impairment in Driving or Use of Machinery

Dementia may cause gradual impairment of driving performance or compromise the ability to use machinery. The administration of rivastigmine may also result in adverse reactions that are detrimental to these functions. During treatment with EXELON PATCH, routinely evaluate the patient's ability to continue driving or operating machinery.

6 ADVERSE REACTIONS

The following clinically significant adverse reactions are described below and elsewhere in the labeling:

- Gastrointestinal Adverse Reactions [see Warnings and Precautions (5.2)]
- Skin Reactions [see Warnings and Precautions (5.3)]
- Other Adverse Reactions from Increased Cholinergic Activity [see Warnings and Precautions (5.4)]

6.1 Clinical Trials Experience

Because clinical trials are conducted under widely varying conditions, adverse reaction rates observed in the clinical trials of a drug cannot be directly compared to rates in the clinical trials of another drug and may not reflect the rates observed in practice.

EXELON PATCH has been administered to 4516 patients with Alzheimer’s disease during clinical trials worldwide. Of these, 3005 patients have been treated for at least 26 weeks, 1771 patients have been treated for at least 52 weeks, 974 patients have been treated for at least 78 weeks, and 24 patients have been treated for at least 104 weeks.

Mild-to-Moderate Alzheimer’s Disease

24-Week International Placebo-Controlled Trial (Study 1)

Most Common Adverse Reactions

The most common adverse reactions in patients administered EXELON PATCH in Study 1 [see Clinical Studies (14)], defined as those occurring at a frequency of at least 5% in the 9.5 mg/24 hours EXELON PATCH arm and at a frequency at higher than in the placebo group, were nausea, vomiting, and diarrhea. These reactions were dose-related, with each being more common in patients using the unapproved 17.4 mg/24 hours EXELON PATCH than in those using the 9.5 mg/24 hours EXELON PATCH.

Discontinuation Rates

In Study 1, which randomized a total of 1195 patients, the proportions of patients in the EXELON PATCH 9.5 mg/24 hours, EXELON Capsules 6 mg twice daily, and placebo groups who discontinued treatment due to adverse events were 10%, 8%, and 5%, respectively.

The most common adverse reactions in the EXELON PATCH-treated groups that led to treatment discontinuation in this study were nausea and vomiting. The proportions of patients who discontinued treatment due to nausea were 0.7%, 1.7%, and 1.3% in the EXELON PATCH 9.5 mg/24 hours, EXELON Capsules 6 mg twice daily, and placebo groups, respectively. The proportions of patients who discontinued treatment due to vomiting were 0%, 2.0%, and 0.3% in the EXELON PATCH 9.5 mg/24 hours, EXELON Capsules 6 mg twice daily, and placebo groups, respectively.

Adverse Reactions Observed at an Incidence of Greater than or Equal to 2%

Table 1 lists adverse reactions seen at an incidence of greater than or equal to 2% in either EXELON PATCH-treated group in Study 1, and for which the rate of occurrence was greater for patients treated with that dose of EXELON PATCH than for those treated with placebo. The unapproved 17.4 mg/24 hours EXELON PATCH arm is included to demonstrate the increased rates of gastrointestinal adverse reactions over those seen with the 9.5 mg/24 hours EXELON PATCH.

Table 1: Proportion of Adverse Reactions Observed With a Frequency of Greater Than or Equal to 2% and Occurring at a Rate Greater Than Placebo in Study 1
Adverse reaction | EXELON PATCH 9.5 mg/24 hours | EXELON PATCH 17.4 mg/24 hours | EXELON Capsule 6 mg twice daily | Placebo
Total patients studied | 291 | 303 | 294 | 302
Total percentage of patients with ARs (%) | 51 | 66 | 63 | 46
Nausea | 7 | 21 | 23 | 5
Vomiting* | 6 | 19 | 17 | 3
Diarrhea | 6 | 10 | 5 | 3
Depression | 4 | 4 | 4 | 1
Headache | 3 | 4 | 6 | 2
Anxiety | 3 | 3 | 2 | 1
Anorexia/Decreased appetite | 3 | 9 | 9 | 2
Weight decreased** | 3 | 8 | 5 | 1
Dizziness | 2 | 7 | 7 | 2
Abdominal pain | 2 | 4 | 1 | 1
Urinary tract infection | 2 | 2 | 1 | 1
Asthenia | 2 | 3 | 6 | 1
Fatigue | 2 | 2 | 1 | 1
Insomnia | 1 | 4 | 2 | 2
Abdominal pain upper | 1 | 3 | 2 | 2
Vertigo | 0 | 2 | 1 | 1
Abbreviation: ARs, adverse reactions.
*Vomiting was severe in 0% of patients who received EXELON PATCH 9.5 mg/24 hours, 1% of patients who received EXELON PATCH 17.4 mg/24 hours, 1% of patients who received the EXELON Capsule at doses up to 6 mg twice daily, and 0% of those who received placebo.
**Weight Decreased as presented in Table 1 is based upon clinical observations and/or adverse events reported by patients or caregivers. Body weight was also monitored at prespecified time points throughout the course of the clinical study. The proportion of patients who had weight loss equal to or greater than 7% of their baseline weight was 8% of those treated with EXELON PATCH 9.5 mg/24 hours, 12% of those treated with EXELON PATCH 17.4 mg/24 hours, 11% of patients who received the EXELON Capsule at doses up to 6 mg twice daily and 6% of those who received placebo. It is not clear how much of the weight loss was associated with anorexia, nausea, vomiting, and the diarrhea associated with the drug.

48-Week International Active Comparator-Controlled Trial (Study 2)

Most Common Adverse Reactions

In Study 2 [see Clinical Studies (14)] of the commonly observed adverse reactions (greater than or equal to 3% in any treatment group), the most frequent event in the EXELON PATCH 13.3 mg/24 hours group was nausea, followed by vomiting, fall, weight decreased, application-site erythema, decreased appetite, diarrhea and urinary tract infection (Table 3). The percentage of patients with these events was higher in the EXELON PATCH 13.3 mg/24 hours group than in the EXELON PATCH 9.5 mg/24 hours group. Patients with nausea, vomiting, diarrhea and decreased appetite experienced these reactions more often during the first 4 weeks of the double-blind treatment phase. These reactions decreased over time in each treatment group. Weight decreased was reported to have increased over time in each treatment group.

Discontinuation Rates

Table 2 displays the most common adverse reactions leading to discontinuation during the 48-week, double-blind treatment phase in Study 2.

Table 2: Proportion of Most Common Adverse Reactions (Greater Than 1% at any Dose) Leading to Discontinuation During 48-week Double-Blind Treatment Phase in Study 2
Adverse reaction | EXELON PATCH 13.3 mg/24 hours | EXELON PATCH 9.5 mg/24 hours | Total
Total patients studied | 280 | 283 | 563
Total percentage of patients with ARs leading to discontinuation (%) | 9.6 | 12.7 | 11.2
Vomiting | 1.4 | 0.4 | 0.9
Application-site pruritus | 1.1 | 1.1 | 1.1
Aggression | 0.4 | 1.1 | 0.7
Abbreviation: ARs, adverse reactions.

Most Common Adverse Reactions Greater than or Equal to 3%

Other adverse reactions of interest which occurred less frequently, but which were observed in a markedly higher percentage of patients in the EXELON PATCH 13.3 mg/24 hours group than in the EXELON PATCH 9.5 mg/24 hours group in Study 2, included dizziness and upper abdominal pain. The percentage of patients with these reactions decreased over time in each treatment group (Table 3). The adverse reaction severity profile was generally similar for both the EXELON PATCH 13.3 mg/24 hours and 9.5 mg/24 hours groups.

Table 3: Proportion of Adverse Reactions Over Time in the 48-week Double-Blind Treatment Phase (at least 3% in any Treatment Group) in Study 2
 | Cumulative Week 0 to 48 (DB Phase) |  | Week 0 to 24 (DB Phase) |  | Week > 24 to 48 (DB Phase)
Adverse reaction | EXELON PATCH 13.3 mg/24 hours | EXELON PATCH 9.5 mg/24 hours | EXELON PATCH 13.3 mg/24 hours | EXELON PATCH 9.5 mg/24 hours | EXELON PATCH 13.3 mg/24 hours | EXELON PATCH 9.5 mg/24 hours
Total patients studied | 280 | 283 | 280 | 283 | 241 | 246
Total percentage of patients with ARs (%) | 75 | 68 | 65 | 55 | 42 | 40
Nausea | 12 | 5 | 10 | 4 | 4 | 2
Vomiting | 10 | 5 | 9 | 3 | 3 | 2
Fall | 8 | 6 | 4 | 4 | 4 | 3
Weight decreased* | 7 | 3 | 3 | 1 | 5 | 2
Application-site erythema | 6 | 6 | 6 | 5 | 1 | 2
Decreased appetite | 6 | 3 | 5 | 2 | 2 | < 1
Diarrhea | 6 | 5 | 5 | 4 | 2 | < 1
Urinary tract infection | 5 | 4 | 3 | 3 | 3 | 2
Agitation | 5 | 5 | 4 | 3 | 1 | 2
Depression | 5 | 5 | 3 | 3 | 3 | 2
Dizziness | 4 | 1 | 3 | < 1 | 2 | < 1
Application-site pruritus | 4 | 4 | 4 | 3 | < 1 | 1
Headache | 4 | 4 | 4 | 4 | < 1 | < 1
Insomnia | 4 | 3 | 2 | 1 | 3 | 2
Abdominal pain upper | 4 | 1 | 3 | 1 | 1 | < 1
Anxiety | 4 | 3 | 2 | 2 | 2 | 1
Hypertension | 3 | 3 | 3 | 2 | 1 | 1
Urinary incontinence | 3 | 2 | 2 | 1 | 1 | < 1
Psychomotor hyperactivity | 3 | 3 | 2 | 3 | 2 | 1
Aggression | 2 | 3 | 1 | 3 | 1 | 1
Abbreviations: DB, double blind; ARs, adverse reactions.
*Decreased Weight as presented in Table 3 is based upon clinical observations and/or adverse events reported by patients or caregivers. Body weight was monitored as a vital sign at pre-specified time points throughout the course of the clinical study. The proportion of patients who had weight loss equal to or greater than 7% of their baseline weight was 15.2% of those treated with EXELON PATCH 9.5 mg/24 hours and 18.6% of those treated with EXELON PATCH 13.3 mg/24 hours during the 48-week double-blind treatment period.

Severe Alzheimer’s Disease

24-Week US Controlled Trial (Study 3)

Most Commonly Observed Adverse Reactions

The most common adverse reactions in patients administered EXELON PATCH in the controlled clinical trial, defined as those occurring at a frequency of at least 5% in the 13.3 mg/24 hours EXELON PATCH arm and at a frequency higher than in the 4.6 mg/24 hours EXELON PATCH were application-site erythema, fall, insomnia, vomiting, diarrhea, weight decreased, and nausea (Table 4). Patients in the lower-dose group reported more events of agitation, urinary tract infection, and hallucinations than patients in the higher-dose group.

Discontinuation Rates

In Study 3 [see Clinical Studies (14)], the proportions of patients in the EXELON PATCH 13.3 mg/24 hours (n = 355) and EXELON PATCH 4.6 mg/24 hours (n = 359), who discontinued treatment due to adverse reactions were 21% and 14%, respectively.

The most frequent adverse reaction leading to discontinuation in the 13.3 mg/24 hours treatment group versus the 4.6 mg/24 hours treatment group was agitation (2.8% versus 2.2%), followed by vomiting (2.5% and 1.1%), nausea (1.7% and 1.1%), decreased appetite (1.7% and 0%), aggression (1.1% and 0.3%), fall (1.1% and 0.3%) and syncope (1.1% and 0.3%). Otherwise, all AEs leading to discontinuation were reported in less than 1% of patients.

Most Commonly Observed Adverse Reactions Greater than or Equal to 5%

Other adverse reactions of interest, which were observed in a higher percentage of patients in the EXELON PATCH 13.3 mg/24 hours group than in the EXELON PATCH 4.6 mg/24 hours group, included application-site erythema, fall, insomnia, vomiting, diarrhea, weight decreased, and nausea (Table 4). Overall, the majority of patients in this study experienced adverse reactions that were mild (30.7%) or moderate (32.1%) in severity. Slightly more patients in the 4.6 mg/24 hours patch group reported mild events than in the 13.3 mg/24 hours patch group, while the numbers of patients reporting moderate events were comparable between groups. Severe adverse reactions were reported at a slightly higher percentage at the higher dose (12.4%) than at the lower-dose (10%) treatment groups. With the exception of severe adverse reactions of agitation (13.3 mg: 1.1%; 4.6 mg: 1.4%), fall (13.3 mg: 1.1%) and urinary tract infection (4.6 mg: 1.1%), all adverse reactions reported as severe occurred in less than 1% of patients in either treatment group.

Table 4: Proportion of Adverse Reactions in the 24-week Double-BlindTreatment Phase (at least 5% in any Treatment Group) in Study 3
Adverse reaction | EXELON PATCH 13.3 mg/24 hours | EXELON PATCH 4.6 mg/24 hours
Total number of patients studied | 355 | 359
Total percentage of patients with ARs (%) | 75 | 73
Application-site erythema | 13 | 12
Agitation | 12 | 14
Urinary tract infection | 8 | 10
Fall | 8 | 6
Insomnia | 7 | 4
Vomiting | 7 | 3
Diarrhea | 7 | 5
Weight decreased* | 7 | 3
Nausea | 6 | 3
Depression | 5 | 4
Decreased appetite | 5 | 1
Anxiety | 5 | 5
Hallucination | 2 | 5
Abbreviation: ARs, adverse reactions.
*Weight Decreased as presented in Table 4 is based upon clinical observations and/or adverse events reported by patients or caregivers. Body weight was monitored as a vital sign at prespecified time points throughout the course of the clinical study. The proportion of patients who had weight loss equal to or greater than 7% of their baseline weight was 11% of those treated with EXELON PATCH 4.6 mg/24 hours and 14.1% of those treated with EXELON PATCH 13.3 mg/24 hours during the 24-week double-blind treatment.

Application-Site Reactions

Application-site skin reactions leading to discontinuation were observed in less than or equal to 2.3% of EXELON PATCH patients. This number was 4.9% and 8.4% in the Chinese population and Japanese population, respectively.

Cases of skin irritation were captured separately on an investigator-rated skin irritation scale. Skin irritation, when observed, was mostly slight or mild in severity and was rated as severe in less than or equal to 2.2% of EXELON PATCH patients in a double-blind controlled study and in less than or equal to 3.7% of EXELON PATCH patients in a double-blind controlled study in Japanese patients.

Parkinson’s Disease Dementia

76-week International Open-Label Trial (Study 4)

EXELON PATCH has been administered to 288 patients with mild-to-moderate Parkinson’s Disease Dementia in a single, 76-week, open-label, active-comparator safety study. Of these, 256 have been treated for at least 12 weeks, 232 for at least 24 weeks, and 196 for at least 52 weeks.

Treatment with EXELON PATCH was initiated at 4.6 mg/24 hours and if tolerated the dose was increased after 4 weeks to 9.5 mg/24 hours. EXELON Capsule (target maintenance dose of 12 mg/day) served as the active comparator and was administered to 294 patients. Adverse reactions are presented in Table 5.

Table 5: Proportion of Adverse Reactions Reported at a Rate Greater Than or Equal to 2% During the Initial 24-Week Period in Study 4
Adverse reaction | EXELON PATCH
Total patients studied | 288
 | Percentage (%)
Psychiatric disorders
Insomnia | 6
Depression | 6
Anxiety | 5
Agitation | 3
Nervous system disorders
Tremor | 7
Dizziness | 6
Somnolence | 4
Hypokinesia | 4
Bradykinesia | 4
Cogwheel rigidity | 3
Dyskinesia | 3
Gastrointestinal disorders
Abdominal pain | 2
Vascular disorders
Hypertension | 3
General disorders and administration-site conditions
Fall | 12
Application-site erythema | 11
Application-site irritation, pruritus, rash | 3; 5; 2
Fatigue | 4
Asthenia | 2
Gait disturbance | 4

Additional adverse reactions observed during the 76-week prospective, open-label study in patients with dementia associated with Parkinson’s disease treated with EXELON PATCH: Frequent (those occurring in at least 1/100 patients): dehydration, weight decreased, aggression, hallucination visual.

In patients with dementia associated with Parkinson’s disease, the following adverse drug reactions have only been observed in clinical trials with EXELON Capsules: Frequent: nausea, vomiting, decreased appetite, restlessness, worsening of Parkinson’s disease, bradycardia, diarrhea, dyspepsia, salivary hypersecretion, sweating increased; Infrequent (those occurring between 1/100 to 1/1000 patients): dystonia, atrial fibrillation, atrioventricular block.

6.2 Postmarketing Experience

The following adverse reactions have been identified during post approval use of EXELON Capsules, EXELON Oral Solution, or EXELON PATCH. Because these reactions are reported voluntarily from a population of uncertain size, it is not always possible to reliably estimate their frequency or establish a causal relationship to drug exposure.

Cardiac Disorders: Tachycardia, QTc prolongation, torsades de pointes

Hepatobiliary Disorders: Abnormal liver function tests, hepatitis

Nervous System Disorders: Parkinson’s disease (worsening), seizure, tremor

Psychiatric Disorders: nightmares

Skin and Subcutaneous Tissue Disorders: Allergic dermatitis, application-site hypersensitivity, blister, disseminated allergic dermatitis, Stevens-Johnson syndrome, urticaria

Vascular Disorders: Hypertension

7 DRUG INTERACTIONS

7.1 Metoclopramide

Due to the risk of additive extra-pyramidal adverse reactions, the concomitant use of metoclopramide and EXELON PATCH is not recommended.

7.2 Cholinomimetic and Anticholinergic Medications

EXELON PATCH may increase the cholinergic effects of other cholinomimetic medications and may also interfere with the activity of anticholinergic medications (e.g., oxybutynin, tolterodine). Concomitant use of EXELON PATCH with medications having these pharmacologic effects is not recommended unless deemed clinically necessary [see Warnings and Precautions (5.5)].

7.3 Beta-Blockers

Additive bradycardic effects resulting in syncope may occur when EXELON is used concomitantly with beta-blockers, especially cardioselective beta-blockers (including atenolol). Concomitant use is not recommended when signs of bradycardia, including syncope are present.

8 USE IN SPECIFIC POPULATIONS

8.1 Pregnancy

Risk Summary

There are no adequate data on the developmental risks associated with the use of EXELON in pregnant women. In animals, no adverse effects on embryo-fetal development were observed at oral doses 2-4 times the maximum recommended human dose (MRHD) (see Data).

The background risk of major birth defects and miscarriage for the indicated population is unknown. In the U.S. general population, the estimated background risk of major birth defects and miscarriage in clinically recognized pregnancies is 2%-4% and 15%-20%, respectively.

Data

Animal Data

Oral administration of rivastigmine to pregnant rats and rabbits throughout organogenesis produced no adverse effects on embryo-fetal development up to the highest dose tested (2.3 mg/kg/day), which is 2 and 4 times, respectively, the MRHD of 12 mg per day on a body surface area (mg/m^2) basis.

8.2 Lactation

Risk Summary

There are no data on the presence of rivastigmine in human milk, the effects on the breastfed infant, or the effects of rivastigmine on milk production. Rivastigmine and its metabolites are excreted in rat milk following oral administration of rivastigmine; levels of rivastigmine plus metabolites in rat milk are approximately 2 times that in maternal plasma.

The developmental and health benefits of breastfeeding should be considered along with the mother’s clinical need for EXELON and any potential adverse effects on the breastfed infant from EXELON or from the underlying maternal condition.

8.4 Pediatric Use

Safety and effectiveness in pediatric patients have not been established. The use of EXELON PATCH in pediatric patients (below 18 years of age) is not recommended.

8.5 Geriatric Use

Of the total number of patients in clinical studies of EXELON PATCH, 88% were 65 years and over, while 55% were 75 years. No overall differences in safety or effectiveness were observed between these patients and younger patients, and other reported clinical experience has not identified differences in responses between the elderly and younger patients, but greater sensitivity of some older individuals cannot be ruled out.

8.6 Hepatic Impairment

Increased exposure to rivastigmine was observed in patients with mild or moderate hepatic impairment with oral rivastigmine. Patients with mild or moderate hepatic impairment may be able to only tolerate lower doses [see Dosage and Administration (2.2), Clinical Pharmacology (12.3)]. No data are available on the use of rivastigmine in patients with severe hepatic impairment.

8.7 Low or High Body Weight

Because rivastigmine blood levels vary with weight, careful titration and monitoring should be performed in patients with low or high body weights [see Dosage and Administration (2.2), Clinical Pharmacology (12.3)].

10 OVERDOSAGE

Overdose with EXELON PATCH has been reported in the postmarketing setting [see Warnings and Precautions (5.1)]. Overdoses have occurred from application of more than one patch at one time and not removing the previous day’s patch before applying a new patch. The symptoms reported in these overdose cases are similar to those seen in cases of overdose associated with rivastigmine oral formulations.

Because strategies for the management of overdose are continually evolving, it is advisable to contact a Poison Control Center to determine the latest recommendations for the management of an overdose of any drug. As rivastigmine has a plasma half-life of about 3.4 hours after patch administration and a duration of acetylcholinesterase inhibition of about 9 hours, it is recommended that in cases of asymptomatic overdose the patch should be immediately removed and no further patch should be applied for the next 24 hours.

As in any case of overdose, general supportive measures should be utilized.

Overdosage with cholinesterase inhibitors can result in cholinergic crisis characterized by severe nausea, vomiting, salivation, sweating, bradycardia, hypotension, respiratory depression, and convulsions. Increasing muscle weakness is a possibility and may result in death if respiratory muscles are involved. Atypical responses in blood pressure and heart rate have been reported with other drugs that increase cholinergic activity when coadministered with quaternary anticholinergics, such as glycopyrrolate. Additional symptoms associated with rivastigmine overdose are diarrhea, abdominal pain, dizziness, tremor, headache, somnolence, confusional state, hyperhidrosis, hypertension, hallucinations and malaise. Due to the short plasma elimination half-life of rivastigmine after patch administration, dialysis (hemodialysis, peritoneal dialysis, or hemofiltration) would not be clinically indicated in the event of an overdose.

In overdose accompanied by severe nausea and vomiting, the use of antiemetics should be considered. A fatal outcome has rarely been reported with rivastigmine overdose.

11 DESCRIPTION

EXELON PATCH (rivastigmine transdermal system) contains rivastigmine, a reversible cholinesterase inhibitor known chemically as (S)-3-[1-(dimethylamino) ethyl]phenyl ethylmethylcarbamate. It has an empirical formula of C14H22N2O2 as the base and a molecular weight of 250.34 g/mol (as the base). Rivastigmine is a viscous, clear, and colorless to yellow to very slightly brown liquid that is sparingly soluble in water and very soluble in ethanol, acetonitrile, n-octanol and ethyl acetate.

The distribution coefficient at 37°C in n-octanol/phosphate buffer solution pH 7 is 4.27.

EXELON PATCH is for transdermal administration. The patch is a 4-layer laminate containing the backing layer, drug matrix, adhesive matrix and overlapping release liner (see Figure 1). The release liner is removed and discarded prior to use.

Figure 1: Cross Section of the EXELON PATCH

Layer 1: | Backing Film
Layer 2: | Drug Product (Acrylic) Matrix
Layer 3: | Adhesive (Silicone) Matrix
Layer 4: | Release Liner (removed at time of use)

Excipients within the formulation include acrylic copolymer, poly (butylmethacrylate, methylmethacrylate), silicone adhesive applied to a flexible polymer backing film, silicone oil, and vitamin E.

12 CLINICAL PHARMACOLOGY

12.1 Mechanism of Action

Although the precise mechanism of action of rivastigmine is unknown, it is thought to exert its therapeutic effect by enhancing cholinergic function. This is accomplished by increasing the concentration of acetylcholine through reversible inhibition of its hydrolysis by cholinesterase. The effect of rivastigmine may lessen as the disease process advances and fewer cholinergic neurons remain functionally intact. There is no evidence that rivastigmine alters the course of the underlying dementing process.

12.2 Pharmacodynamics

After a 6-mg oral dose of rivastigmine in humans, anticholinesterase activity is present in cerebrospinal fluid for about 10 hours, with a maximum inhibition of about 60% 5 hours after dosing.

In vitro and in vivo studies demonstrate that the inhibition of cholinesterase by rivastigmine is not affected by the concomitant administration of memantine, an N-methyl-D-aspartate receptor antagonist.

12.3 Pharmacokinetics

Absorption

After the initial application of EXELON PATCH, there is a lag time of 0.5 to 1 hour in the absorption of rivastigmine. Concentrations then rise slowly typically reaching a maximum after 8 hours, although maximum values (Cmax) can also occur later (at 10 to 16 hours). After the peak, plasma concentrations slowly decrease over the remainder of the 24-hour period of application. At steady state, trough levels are approximately 60% to 80% of peak levels.

EXELON PATCH 9.5 mg/24 hours gave exposure approximately the same as that provided by an oral dose of 6 mg twice daily (i.e., 12 mg/day). Inter-subject variability in exposure was lower (43% to 49%) for the EXELON PATCH formulation as compared with the oral formulations (73% to 103%). Fluctuation (between Cmax and Cmin) is less for EXELON PATCH than for the oral formulation of rivastigmine.

Figure 2 displays rivastigmine plasma concentrations over 24 hours for the 3 available patch strengths.

Figure 2: Rivastigmine Plasma Concentrations Following Dermal 24-Hour Patch Application

Over a 24-hour dermal application, approximately 50% of the drug content of the patch is released from the system.

Exposure area under the plasma concentration-time curve from time zero to infinity (AUC∞) to rivastigmine (and metabolite NAP226-90) was highest when the patch was applied to the upper back, chest, or upper arm. Two other sites (abdomen and thigh) could be used if none of the 3 other sites is available, but the practitioner should be aware that the rivastigmine plasma exposure associated with these sites was approximately 20% to 30% lower.

There was no relevant accumulation of rivastigmine or the metabolite NAP226-90 in plasma in patients with Alzheimer’s disease with daily dosing.

The pharmacokinetic profile of rivastigmine transdermal patches was comparable in patients with Alzheimer’s disease and in patients with dementia associated with Parkinson’s disease.

Distribution

Rivastigmine is weakly bound to plasma proteins (approximately 40%) over the therapeutic range. It readily crosses the blood-brain barrier, reaching CSF peak concentrations in 1.4 to 2.6 hours. It has an apparent volume of distribution in the range of 1.8 to 2.7 L/kg.

Metabolism

Rivastigmine is extensively metabolized primarily via cholinesterase-mediated hydrolysis to the decarbamylated metabolite NAP226-90. In vitro, this metabolite shows minimal inhibition of acetylcholinesterase (less than 10%). Based on evidence from in vitro and animal studies, the major cytochrome P450 isoenzymes are minimally involved in rivastigmine metabolism.

The metabolite-to-parent AUC∞ ratio was about 0.7 after EXELON PATCH application versus 3.5 after oral administration, indicating that much less metabolism occurred after dermal treatment. Less NAP226-90 is formed following patch application, presumably because of the lack of presystemic (hepatic first pass) metabolism. Based on in vitro studies, no unique metabolic routes were detected in human skin.

Elimination

Renal excretion of the metabolites is the major route of elimination. Unchanged rivastigmine is found in trace amounts in the urine. Following administration of ^14C-rivastigmine, renal elimination was rapid and essentially complete (greater than 90%) within 24 hours. Less than 1% of the administered dose is excreted in the feces. The apparent elimination half-life in plasma is approximately 3 hours after patch removal. Renal clearance was approximately 2.1 to 2.8 L/hr.

Age

Age had no impact on the exposure to rivastigmine in Alzheimer’s disease patients treated with EXELON PATCH.

Gender and Race

No specific pharmacokinetic study was conducted to investigate the effect of gender and race on the disposition of EXELON PATCH. A population pharmacokinetic analysis of oral rivastigmine indicated that neither gender (n = 277 males and 348 females) nor race (n = 575 Caucasian, 34 black, 4 Asian, and 12 Other) affected clearance of the drug. Similar results were seen with analyses of pharmacokinetic data obtained after the administration of EXELON PATCH.

Body Weight

A relationship between drug exposure at steady state (rivastigmine and metabolite NAP226-90) and body weight was observed in Alzheimer’s dementia patients. Rivastigmine exposure is higher in subjects with low body weight. Compared to a patient with a body weight of 65 kg, the rivastigmine steady-state concentrations in a patient with a body weight of 35 kg would be approximately doubled, while for a patient with a body weight of 100 kg the concentrations would be approximately halved [see Dosage and Administration (2.2)].

Renal Impairment

No study was conducted with EXELON PATCH in subjects with renal impairment. Based on population analysis, creatinine clearance did not show any clear effect on steady-state concentrations of rivastigmine or its metabolite.

Hepatic Impairment

No pharmacokinetic study was conducted with EXELON PATCH in subjects with hepatic impairment. Following a single 3-mg dose, mean oral clearance of rivastigmine was 60% lower in hepatically impaired patients (n = 10, biopsy proven) than in healthy subjects (n = 10). After multiple 6-mg twice a day oral dosing, the mean clearance of rivastigmine was 65% lower in mild (n = 7, Child-Pugh score 5 to 6) and moderate (n = 3, Child-Pugh score 7 to 9) hepatically impaired patients (biopsy proven, liver cirrhosis) than in healthy subjects (n = 10) [see Dosage and Administration (2.2), Use in Specific Populations (8.6)].

Smoking

Following oral rivastigmine administration (up to 12 mg/day) with nicotine use, population pharmacokinetic analysis showed increased oral clearance of rivastigmine by 23% (n = 75 smokers and 549 nonsmokers).

Drug Interaction Studies

No specific interaction studies have been conducted with EXELON PATCH. Information presented below is from studies with oral rivastigmine.

Effect of Rivastigmine on the Metabolism of Other Drugs

Rivastigmine is primarily metabolized through hydrolysis by esterases. Minimal metabolism occurs via the major cytochrome P450 isoenzymes. Based on in vitro studies, no pharmacokinetic drug interactions with drugs metabolized by the following isoenzyme systems are expected: CYP1A2, CYP2D6, CYP3A4/5, CYP2E1, CYP2C9, CYP2C8, CYP2C19, or CYP2B6.

No pharmacokinetic interaction was observed between rivastigmine taken orally and digoxin, warfarin, diazepam, or fluoxetine in studies in healthy volunteers. The increase in prothrombin time induced by warfarin is not affected by administration of rivastigmine.

Effect of Other Drugs on the Metabolism of Rivastigmine

Drugs that induce or inhibit CYP450 metabolism are not expected to alter the metabolism of rivastigmine.

Population pharmacokinetic analysis with a database of 625 patients showed that the pharmacokinetics of rivastigmine taken orally were not influenced by commonly prescribed medications, such as antacids (n = 77), antihypertensives (n = 72), beta-blockers (n = 42), calcium channel blockers (n = 75), antidiabetics (n = 21), nonsteroidal anti-inflammatory drugs (n = 79), estrogens (n = 70), salicylate analgesics (n = 177), antianginals (n = 35), and antihistamines (n = 15).

13 NONCLINICAL TOXICOLOGY

13.1 Carcinogenesis, Mutagenesis, Impairment of Fertility

Carcinogenesis

In oral carcinogenicity studies conducted at doses up to 1.1 mg/kg/day in rats and 1.6 mg/kg/day in mice, rivastigmine was not carcinogenic.

In a dermal carcinogenicity study conducted at doses up to 0.75 mg base/kg/day in mice, rivastigmine was not carcinogenic. The mean rivastigmine plasma exposure (AUC) at this dose was less than that in humans at the maximum recommended human dose (13.3 mg/24 hours).

Mutagenesis

Rivastigmine was clastogenic in in vitro chromosomal aberration assays in mammalian cells in the presence, but not the absence, of metabolic activation. Rivastigmine was negative in an in vitro bacterial reverse mutation (Ames) assay, an in vitro HGPRT assay, and in an in vivo mouse micronucleus test.

Impairment of Fertility

No fertility or reproduction studies of dermal rivastigmine have been conducted in animals. Rivastigmine had no effect on fertility or reproductive performance in rats at oral doses up to 1.1 mg/kg/day.

14 CLINICAL STUDIES

The effectiveness of the EXELON PATCH in dementia of the Alzheimer’s type and dementia associated with Parkinson’s disease was based on the results of 3 controlled trials of EXELON PATCH in patients with Alzheimer’s disease (Studies 1, 2, and 3) (see below); 3 controlled trials of oral rivastigmine in patients with dementia of the Alzheimer’s type; and 1 controlled trial of oral rivastigmine in patients with dementia associated with Parkinson’s disease. See the prescribing information for oral rivastigmine for details of the four studies of oral rivastigmine.

Mild-to-Moderate Alzheimer’s Disease

International 24-Week Study of EXELON PATCH in Dementia of the Alzheimer’s Type (Study 1)

This study was a randomized double-blind, double dummy clinical investigation in patients with Alzheimer’s disease [diagnosed by NINCDS-ADRDA and DSM-IV criteria, Mini-Mental Status Examination (MMSE) score greater than or equal to 10 and less than or equal to 20] (Study 1). The mean age of patients participating in this trial was 74 years with a range of 50 to 90 years. Approximately 67% of patients were women, and 33% were men. The racial distribution was Caucasian 75%, black 1%, Asian 9%, and other races 15%.

The effectiveness of the EXELON PATCH was evaluated in Study 1 using a dual outcome assessment strategy, evaluating for changes in both cognitive performance and overall clinical effect.

The ability of the EXELON PATCH to improve cognitive performance was assessed with the cognitive subscale of the Alzheimer’s Disease Assessment Scale (ADAS-Cog), a multi-item instrument that has been extensively validated in longitudinal cohorts of Alzheimer’s-disease patients. The ADAS-Cog examines selected aspects of cognitive performance, including elements of memory, orientation, attention, reasoning, language, and praxis. The ADAS-Cog scoring range is from 0 to 70, with higher scores indicating greater cognitive impairment. Elderly normal adults may score as low as 0 or 1, but it is not unusual for non-demented adults to score slightly higher.

The ability of the EXELON PATCH to produce an overall clinical effect was assessed using the Alzheimer’s Disease Cooperative Study-Clinical Global Impression of Change (ADCS-CGIC). The ADCS-CGIC is a more standardized form of the Clinician's Interview-Based Impression of Change-Plus (CIBIC-Plus) and is also scored as a 7-point categorical rating; scores range from 1, indicating “markedly improved,” to 4, indicating “no change,” to 7, indicating “marked worsening.”

In Study 1, 1195 patients were randomized to 1 of the following 4 treatments: EXELON PATCH 9.5 mg/24 hours, EXELON PATCH 17.4 mg/24 hours, EXELON Capsules in a dose of 6 mg twice daily, or placebo. This 24-week study was divided into a 16-week titration phase followed by an 8-week maintenance phase. In the active treatment arms of this study, doses below the target dose were permitted during the maintenance phase in the event of poor tolerability.

Figure 3 illustrates the time course for the change from baseline in ADAS-Cog scores for all 4 treatment groups over the 24-week study. At 24 weeks, the mean differences in the ADAS-Cog change scores for the EXELON-treated patients compared to the patients on placebo, were 1.8, 2.9, and 1.8 units for the EXELON PATCH 9.5 mg/24 hours, EXELON PATCH 17.4 mg/24 hours, and EXELON Capsule 6 mg twice daily groups, respectively. The difference between each of these groups and placebo was statistically significant. Although a slight improvement was observed with the 17.4 mg/24 hours patch compared to the 9.5 mg/24 hours patch on this outcome measure, no meaningful difference between the two was seen on the global evaluation (see Figure 4).

Figure 3: Time Course of the Change from Baseline in ADAS-Cog Score for Patients Observed at Each Time Point in Study 1

Figure 4 presents the distribution of patients’ scores on the ADCS-CGIC for all 4 treatment groups. At 24 weeks, the mean difference in the ADCS-CGIC scores for the comparison of patients in each of the EXELON-treated groups with the patients on placebo was 0.2 units. The difference between each of these groups and placebo was statistically significant.

Figure 4: Distribution of ADCS-CGIC Scores for Patients Completing Study 1

International 48-Week Study of EXELON PATCH in Dementia of the Alzheimer’s Type (Study 2)

This study was a randomized double-blind clinical investigation in patients with Alzheimer’s disease [diagnosed by NINCDS-ADRDA and DSM-IV criteria, Mini-Mental State Examination (MMSE) score greater than or equal to 10 and less than or equal to 24] (Study 2). The mean age of patients participating in this trial was 76 years with a range of 50 to 85 years. Approximately 65% of patients were women and 35% were men. The racial distribution was approximately Caucasian 97%, black 2%, Asian 0.5%, and other races 1%. Approximately 27% of the patients were taking memantine throughout the entire duration of the study.

Alzheimer’s disease patients who received 24 to 48 weeks open-label treatment with EXELON PATCH 9.5 mg/24 hours and who demonstrated functional and cognitive decline were randomized into treatment with either EXELON PATCH 9.5 mg/24 hours or EXELON PATCH 13.3 mg/24 hours in a 48-week, double-blind treatment phase. Functional decline was assessed by the investigator and cognitive decline was defined as a decrease in the MMSE score of greater than or equal to 2 points from the previous visit or a decrease of greater than or equal to 3 points from baseline.

Study 2 was designed to compare the efficacy of EXELON PATCH 13.3 mg/24 hours versus that of EXELON PATCH 9.5 mg/24 hours during the 48-week, double-blind treatment phase.

The ability of the EXELON PATCH 13.3 mg/24 hours to improve cognitive performance over that provided by the EXELON PATCH 9.5 mg/24 hours was assessed by the cognitive subscale of the Alzheimer’s Disease Assessment Scale (ADAS-Cog) [see Clinical Studies (14)].

The ability of the EXELON PATCH 13.3 mg/24 hours to improve overall function versus that provided by EXELON PATCH 9.5 mg/24 hours was assessed by the instrumental subscale of the Alzheimer’s Disease Cooperative Study Activities of Daily Living (ADCS-IADL). The ADCS-IADL subscale is composed of items 7 to 23 of the caregiver-based ADCS-ADL scale. The ADCS-IADL assesses activities, such as those necessary for communicating and interacting with other people, maintaining a household, and conducting hobbies and interests. A sum score is calculated by adding the scores of the individual items and can range from 0 to 56, with higher scores indicating less impairment.

Out of a total of 1584 patients enrolled in the initial open-label phase of the study, 567 patients were classified as decliners and were randomized into the 48-week double-blind treatment phase of the study. Two hundred eighty-seven (287) patients entered the 9.5 mg/24 hours EXELON PATCH treatment group and 280 patients entered the 13.3 mg/24 hours EXELON PATCH treatment group.

Figure 5 illustrates the time course for the mean change from double-blind baseline in ADCS-IADL scores for each treatment group over the course of the 48-week treatment phase of the study. Decline in the mean ADCS-IADL score from the double-blind baseline for the Intent to Treat–Last Observation Carried Forward (ITT-LOCF) analysis was less at each timepoint in the 13.3 mg/24 hour EXELON PATCH treatment group than in the 9.5 mg/24 hours EXELON PATCH treatment group. The 13.3 mg/24 hours dose was statistically significantly superior to the 9.5mg/24 hours dose at weeks 16, 24, 32, and 48 (primary endpoint).

Figure 6 illustrates the time course for the mean change from double-blind baseline in ADAS-Cog scores for both treatment groups over the 48-week treatment phase. The between-treatment group difference for EXELON PATCH 13.3 mg/24 hours versus EXELON PATCH 9.5 mg/24 hours was nominally statistically significant at week 24 (p = 0.027), but not at week 48 (p = 0.227), which was the primary endpoint.

Figure 5: Time Course of the Change From Double-Blind Baseline in ADCS-IADL Score for Patients Observed at Each Time Point in Study 2
Figure 6: Time Course of the Change From Double-Blind Baseline in ADAS-Cog Score for Patients Observed at Each Time Point in Study 2

Severe Alzheimer’s Disease

24-Week United States Study With EXELON PATCH in Severe Alzheimer’s Disease (Study 3)

This was a 24-week randomized double-blind, clinical investigation in patients with severe Alzheimer’s disease [diagnosed by NINCDS-ADRDA and DSM-IV criteria, Mini-Mental State Examination (MMSE) score greater than or equal to 3 and less than or equal to 12]. The mean age of patients participating in this trial was 78 years with a range of 51 to 96 years with 62% aged greater than 75 years. Approximately 65% of patients were women and 35% were men. The racial distribution was approximately Caucasian 87%, black 7%, Asian 1%, and other races 5%. Patients on a stable dose of memantine were permitted to enter the study. Approximately 61% of the patients in each treatment group were taking memantine throughout the entire duration of the study.

The study was designed to compare the efficacy of EXELON PATCH 13.3 mg/24 hours versus that of EXELON PATCH 4.6 mg/24 hours during the 24-week double-blind treatment phase.

The ability of the 13.3 mg/24 hours EXELON PATCH to improve cognitive performance versus that provided by the 4.6 mg/24 hours EXELON PATCH was assessed with the Severe Impairment Battery (SIB) which uses a validated 40-item scale developed for the evaluation of the severity of cognitive dysfunction in more advanced AD patients. The domains assessed included social interaction, memory, language, attention, orientation, praxis, visuospatial ability, construction, and orienting to name. The SIB was scored from 0 to 100, with higher scores reflecting higher levels of cognitive ability.

The ability of the 13.3 mg/24 hours EXELON PATCH to improve overall function versus that provided by the 4.6 mg/24 hours EXELON PATCH was assessed with the Alzheimer’s Disease Cooperative Study-Activities of Daily Living-Severe Impairment Version (ADCS-ADL-SIV) which is a caregiver-based ADL scale composed of 19 items developed for use in clinical studies of dementia. It is designed to assess the patient's performance of both basic and instrumental activities of daily living, such as those necessary for personal care, communicating and interacting with other people, maintaining a household, conducting hobbies and interests, and making judgments and decisions. A sum score is calculated by adding the scores of the individual items and can range from 0 to 54, with higher scores indicating less functional impairment.

In this study, 716 patients were randomized into one of the following treatments: EXELON PATCH 13.3 mg/24 hours or EXELON PATCH 4.6 mg/24 hours in a 1:1 ratio. This 24-week study was divided into an 8-week titration phase followed by a 16-week maintenance phase. In the active treatment arms of this study, temporary dose adjustments below the target dose were permitted during the titration and maintenance phase in the event of poor tolerability.

Figure 7 illustrates the time course for the mean change from baseline SIB scores for each treatment group over the course of the 24-week treatment phase of the study. Decline in the mean SIB score from the baseline for the Modified Full Analysis Set (MFAS)-Last Observation Carried Forward (LOCF) analysis was less at each timepoint in the 13.3 mg/24 hours EXELON PATCH treatment group than in the 4.6 mg/24 hours EXELON PATCH treatment group. The 13.3 mg/24 hours dose was statistically significantly superior to the 4.6 mg/24 hours dose at weeks 16 and 24 (primary endpoint).

Figure 8 illustrates the time course for the mean change from baseline in ADCS-ADL-SIV scores for each treatment group over the course of the 24-week treatment phase of the study. Decline in the mean ADCS-ADL-SIV score from baseline for the MFAS-LOCF analysis was less at each timepoint in the 13.3 mg/24 hours EXELON PATCH treatment group than in the 4.6 mg/24 hours EXELON PATCH treatment group. The 13.3 mg/24 hours dose was statistically significantly superior to the 4.6 mg/24 hours dose at weeks 16 and 24 (primary endpoint).

Figure 7: Time Course of the Change From Baseline in SIB Score for Patients Observed at Each Time Point (Modified Full Analysis Set-LOCF)
Figure 8: Time Course of the Change From Baseline in ADCS-ADL-SIV Score for Patients Observed at Each Time Point (Modified Full Analysis Set-LOCF)

16 HOW SUPPLIED/STORAGE AND HANDLING

EXELON PATCH: 4.6 mg/24 hours

Each patch of 5 cm^2 contains 9 mg rivastigmine base with in vivo release rate of 4.6 mg/24 hours.

Carton of 30………………………NDC 0078-0501-15

EXELON PATCH: 9.5 mg/24 hours

Each patch of 10 cm^2 contains 18 mg rivastigmine base with in vivo release rate of 9.5 mg/24 hours.

Carton of 30………………………..NDC 0078-0502-15

EXELON PATCH: 13.3 mg/24 hours

Each patch of 15 cm^2 contains 27 mg rivastigmine base with in vivo release rate of 13.3 mg/24 hours.

Carton of 30………………………NDC 0078-0503-15

Store at 20°C to 25°C (68°F to 77°F); excursions permitted between 15°C and 30°C (59°F and 86°F) [see USP Controlled Room Temperature]. Keep EXELON PATCH in the individual sealed pouch until use. Each pouch contains 1 patch. Used systems should be folded, with the adhesive surfaces pressed together, and discarded safely.

17 PATIENT COUNSELING INFORMATION

Advise the patient to read the FDA-approved patient labeling (Patient Information and Instructions for Use).

Importance of Correct Usage

Inform patients or caregivers of the importance of applying the correct dose on the correct part of the body. They should be instructed to rotate the application site in order to minimize skin irritation. The same site should not be used within 14 days. The previous day’s patch must be removed before applying a new patch to a different skin location. EXELON PATCH should be replaced every 24 hours and the time of day should be consistent. It may be helpful for this to be part of a daily routine, such as the daily bath or shower. Only 1 patch should be worn at a time [see Dosage and Administration (2.4), Warnings and Precautions (5.1)].

Instruct patients or caregivers to avoid exposure of the patch to external heat sources (excessive sunlight, saunas, solariums) for long periods of time.

Instruct patients who have missed a dose to apply a new patch immediately. They may apply the next patch at the usual time the next day. Instruct patients to not apply 2 patches to make up for 1 missed.

Inform the patient or caregiver to contact the physician for retitration instructions if treatment has been interrupted.

Discarding Used Patches

Instruct patients or caregivers to fold the patch in half after use, return the used patch to its original pouch, and discard it out of the reach and sight of children and pets. They should also be informed that drug still remains in the patch after 24-hour usage. They should be instructed to avoid eye contact and to wash their hands after handling the patch. In case of accidental contact with the eyes, or if their eyes become red after handling the patch, they should be instructed to rinse immediately with plenty of water and to seek medical advice if symptoms do not resolve [see Dosage and Administration (2.4)].

Gastrointestinal Adverse Reactions

Inform patients or caregivers of the potential gastrointestinal adverse reactions, such as nausea, vomiting, and diarrhea, including the possibility of dehydration due to these symptoms. Explain that EXELON PATCH may affect the patient’s appetite and/or the patient’s weight. Patients and caregivers should be instructed to look for these adverse reactions, in particular when treatment is initiated or the dose is increased. Instruct patients and caregivers to inform a physician if these adverse reactions persist [see Warnings and Precautions (5.2)].

Skin Reactions

Inform patients or caregivers about the potential for allergic contact dermatitis reactions to occur. Patients or caregivers should be instructed to inform a physician if application-site reactions spread beyond the patch size, if there is evidence of a more intense local reaction (e.g., increasing erythema, edema, papules, vesicles) and if symptoms do not significantly improve within 48 hours after patch removal [see Warnings and Precautions (5.3)].

Concomitant Use of Drugs With Cholinergic Action

Inform patients or caregivers that while wearing EXELON PATCH, patients should not be taking EXELON Capsules or EXELON Oral Solution or other drugs with cholinergic effects [see Warnings and Precautions (5.4)].

Pregnancy

Advise patients to notify their healthcare provider if they are pregnant or plan to become pregnant.

Distributed by:
Novartis Pharmaceuticals Corporation
East Hanover, New Jersey 07936

Patient Information
EXELON® (ECS-‘el-on) PATCH
(rivastigmine transdermal system)

What is the most important information I should know about EXELON PATCH?
EXELON PATCH is for skin use only.
What is EXELON PATCH?
EXELON PATCH is a prescription medicine used to treat:

- Mild, moderate, and severe memory problems (dementia) associated with Alzheimer’s disease.
- Mild-to-moderate memory problems (dementia) associated with Parkinson’s disease (PD).

Based on clinical trials conducted over 6 to 12 months, EXELON PATCH was shown to help with cognition which includes (memory, understanding communication, and reasoning) and with doing daily tasks. EXELON PATCH does not work the same in all people. Some people treated with EXELON PATCH may:

- Seem much better
- Get better in small ways or stay the same
- Get worse but slower than expected
- Not change and then get worse as expected

Some patients will not benefit from treatment with EXELON Patch. EXELON PATCH does not cure Alzheimer’s disease. All patients with Alzheimer’s disease get worse over time.

EXELON PATCH comes as a transdermal system that delivers rivastigmine (the medicine in EXELON PATCH) through the skin.

It is not known if EXELON PATCH is safe or effective in children under 18 years of age.

Who should not use EXELON PATCH?
Do not use EXELON PATCH if you:

- are allergic to rivastigmine, carbamate derivatives, or any of the ingredients in EXELON PATCH. See the end of this leaflet for a complete list of ingredients in EXELON PATCH.
- have had a skin reaction that:
- spread beyond the EXELON PATCH size
- had blisters, increased skin redness, or swelling
- did not get better within 48 hours after you removed the EXELON PATCH

Ask your healthcare provider if you are not sure if you should use EXELON PATCH.

What should I tell my healthcare provider before using EXELON PATCH?
Before you use EXELON PATCH, tell your healthcare provider if you:

- have or have had a stomach ulcer
- are planning to have surgery
- have or have had problems with your heart
- have problems passing urine
- have or have had seizures
- have problems with movement (tremors)
- have asthma or breathing problems
- have a loss of appetite or are losing weight
- have had a skin reaction to rivastigmine (the medicine in EXELON PATCH) in the past
- have any other medical conditions
- are pregnant or plan to become pregnant. It is not known if the medicine in EXELON PATCH will harm your unborn baby. Talk to your healthcare provider if you are pregnant or plan to become pregnant.
- are breastfeeding or plan to breastfeed. It is not known if the medicine in EXELON PATCH passes into your breast milk. Talk to your doctor about the best way to feed your baby if you take EXELON PATCH.

Tell your healthcare provider about all the medicines you take, including prescription and over-the-counter medicines, vitamins, and herbal supplements.
Especially tell your healthcare provider if you take:

- a medicine used to treat inflammation [nonsteroidal anti-inflammatory drugs (NSAIDs)]
- other medicines used to treat Alzheimer’s or Parkinson’s disease
- an anticholinergic medicine, such as an allergy or cold medicine, a medicine to treat bladder or bowel spasms, or certain asthma medicines, or certain medicines to prevent motion or travel sickness
- metoclopramide, a drug given to relieve symptoms of nausea, gastroesophageal reflux disease (GERD), or nausea and vomiting after surgery or chemotherapy treatment
- If you are undergoing surgery while using EXELON PATCH, inform your doctor because EXELON PATCH may exaggerate the effects of anesthesia, or the effects of a beta-blocker, a type of medicine given for high blood pressure, heart disease, and other medical conditions

Ask your healthcare provider if you are not sure if your medicine is one listed above.

Know the medicines you take. Keep a list of them to show to your healthcare provider and pharmacist when you get a new medicine.

How should I use EXELON PATCH?

- Use EXELON PATCH exactly as your healthcare provider tells you to use it.
- EXELON PATCH comes in 3 different dosage strengths.
- Your healthcare provider may change your dose as needed.
- Wear only 1 EXELON PATCH at a time.
- EXELON Patch is for skin use only.
- Only apply EXELON PATCH to healthy skin that is clean, dry, hairless, and free of redness, irritation, burns or cuts.
- Avoid applying EXELON PATCH to areas on your body that will be rubbed against tight clothing.
- Do not apply EXELON PATCH to skin that has cream, lotion, or powder on it.
- Change your EXELON PATCH every 24 hours at the same time of day. You may write the date and time you put on the EXELON PATCH with a ballpoint pen before applying the patch to help you remember when to remove it.
- Change your application site every day to avoid skin irritation. You can use the same area, but do not use the exact same spot for at least 14 days after your last application.
- Check to see if the EXELON PATCH has become loose when you are bathing, swimming, or showering.
- EXELON PATCH is designed to deliver medication during the time it is worn. If your EXELON PATCH falls off before its usual replacement time, put on a new EXELON PATCH right away. Replace the new patch the next day at the same time as usual. Do not use overlays, bandages, or tape to secure an EXELON PATCH that has become loose or try to reapply an EXELON PATCH that has fallen off.
- If you miss a dose or forget to change your EXELON PATCH, apply your next EXELON PATCH as soon as you remember. Do not apply 2 EXELON PATCHes to make up for the missed dose.
- If you miss more than 3 doses of applying EXELON PATCH, call your healthcare provider before putting on a new EXELON PATCH. You may need to restart EXELON PATCH at a lower dose.
- Always remove the old EXELON PATCH from the previous day before you apply a new one.
- Having more than 1 EXELON PATCH on your body at the same time can cause you to get too much medicine. If you accidentally use more than 1 EXELON PATCH at a time, call your healthcare provider right away. If you are unable to reach your healthcare provider, call your local Poison Control Center at 1-800-222-1222 or go to the nearest hospital emergency room right away.

What should I avoid while using EXELON PATCH?

- Do not touch your eyes after you touch the EXELON PATCH. In case of accidental contact with your eyes or if your eyes become red after handling the patch, rinse immediately with plenty of water and seek medical advice if symptoms do not resolve.
- EXELON PATCH can cause drowsiness, dizziness, weakness, or fainting. Do not drive, operate heavy machinery, or do other dangerous activities until you know how EXELON PATCH affects you.
- Avoid exposure to heat sources, such as excessive sunlight, saunas, or sunrooms for long periods of time.

What are the possible side effects of EXELON PATCH?
EXELON PATCH may cause serious side effects, including:

- Medication overdose. Hospitalization and rarely death may happen when people accidently wear more than 1 patch at the same time. It is important that the old EXELON PATCH be removed before you apply a new one. Do not wear more than 1 EXELON PATCH at a time.
- Stomach or bowel (intestinal) problems, including:
- nausea
- vomiting
- diarrhea
- dehydration
- loss of appetite
- weight loss
- bleeding in your stomach (ulcers)
- Skin reactions. Some people have had a serious skin reaction called allergic contact dermatitis (ACD) when using EXELON PATCH. Stop using EXELON PATCH and call your healthcare provider right away if you experience reactions that spread beyond the patch size, are intense in nature and do not improve within 48 hours after the patch is removed. Symptoms of ACD may be intense and include:
- itching, redness, swelling, warmth or tenderness of the skin
- peeling or blistering of the skin that may ooze, drain or crust over
- Heart problems
- Seizures
- Problems with movement (tremors)

The most common side effects of EXELON PATCH include:

- Depression
- headache
- anxiety
- dizziness
- stomach pain
- urinary tract infections
- muscle weakness
- tiredness
- trouble sleeping

Tell your healthcare provider if you have any side effect that bothers you or that does not go away.

These are not all the possible side effects of EXELON PATCH. For more information, ask your healthcare provider or pharmacist.

Call your doctor for medical advice about side effects. You may report side effects to the FDA at 1-800-FDA-1088.

How should I store EXELON PATCH?

- Store EXELON PATCH between 68°F to 77°F (20°C to 25°C).
- Keep EXELON PATCH in the sealed pouch until ready to use.

Keep EXELON PATCH and all medicines out of the reach of children.

General information about the safe and effective use of EXELON PATCH.

Medicines are sometimes prescribed for purposes other than those listed in the Patient Information leaflet. Do not use EXELON PATCH for a condition for which it was not prescribed. Do not give EXELON PATCH to other people, even if they have the same symptoms you have. It may harm them.

This Patient Information leaflet summarizes the most important information about EXELON PATCH. If you would like more information, talk with your healthcare provider. You can ask your pharmacist or healthcare provider for information about EXELON PATCH that is written for health professionals.

For more information, go to www.EXELONPATCH.com or call 1-888-669-6682.

What are the ingredients of EXELON PATCH?

Active ingredient: rivastigmine

Excipients include: acrylic copolymer, poly (butylmethacrylate, methylmethacrylate), silicone adhesive applied to a flexible polymer backing film, silicone oil, and vitamin E.

Distributed by:
Novartis Pharmaceuticals Corporation
East Hanover, New Jersey 07936

© Novartis

This Patient Information has been approved by the U.S. Food and Drug Administration.

Revised: 6/2020

Instructions for Use

EXELON® (ECS-‘el-on) PATCH

(rivastigmine transdermal system)

You will need the following supplies (See Figure A):

EXELON PATCH is supplied in cartons containing 30 patches (See Figure A)

Figure A

- EXELON PATCH is a thin, beige, plastic patch that sticks to the skin. Each EXELON PATCH is sealed in a pouch that protects it until you are ready to put it on (See Figure A).
- Only 1 EXELON PATCH should be worn at a time. Do not apply more than 1 EXELON PATCH at a time to the body.
- Do not open the pouch or remove the EXELON PATCH until you are ready to apply it.

Using EXELON PATCH:

Step 1. Choose an area to apply the EXELON PATCH (See Figure B).

- Instructions for Caregivers: Apply EXELON PATCH to the upper or lower back if it is likely that the patient will remove it. If this is not a concern, the EXELON PATCH can be applied instead to the upper arm or chest. Do not apply the EXELON PATCH to areas where it can be rubbed off by tight clothing or belts.
- Only apply the EXELON PATCH to healthy skin that is clean, dry, hairless, and free of redness, irritation, burns or cuts.

Figure B

The diagram represents areas on the body where EXELON PATCH may be applied. Only 1 patch should be worn at a time. Do not apply multiple patches to the body.

Step 2. Remove the EXELON PATCH from the pouch (See Figure C).

Carefully cut the pouch along the dotted line to open and remove the EXELON PATCH. Save the pouch for later use.

Figure C

- Do not cut or fold the EXELON PATCH itself.

Step 3. Remove 1 side of the adhesive liner (See Figure D).

- A protective liner covers the sticky (adhesive) side of the EXELON PATCH. Peel off 1 side of the protective cover. Do not touch the sticky part of the EXELON PATCH with your fingers.

Figure D

Step 4. Apply the EXELON PATCH to your skin (See Figure E).

- Apply the sticky (adhesive) side of the EXELON PATCH to your chosen area of skin and then peel off the other side of the protective cover.

Figure E

- Press down on the EXELON PATCH firmly for 30 seconds to make sure that the edges stick to your skin (See Figure F).

Figure F

Step 5: Wash your hands with soap and water right away.

Note:

- If your EXELON PATCH falls off, select a new area, and repeat Steps 2 to 5 to apply a new EXELON PATCH.
- Be sure to replace the new EXELON PATCH the next day at the same time as usual.

Removing your EXELON PATCH:

Step 6. Remove the EXELON PATCH from the skin (See Figure G).

- Gently pull on 1 edge of the EXELON PATCH to remove it from your skin.

Figure G

Throwing away the used EXELON PATCH:

Step 7. Throw away the used EXELON PATCH (See Figure H).

- Fold the used EXELON PATCH in half (with the sticky sides together) and put it back into the pouch that you saved.

Figure H

- Throw away the used EXELON PATCH safely and out of the reach of children and pets.
- Some medicine stays in the patch for 24 hours after you use it and should be folded together (sticky side together) and safely thrown away. Do not try to re-use EXELON PATCHes.

Step 8: Wash your hands with soap and water right away.

- After you remove the EXELON PATCH, if any adhesive remains on your skin, you can use soap and water or an oil-based substance (such as baby oil) to remove the adhesive. Alcohol or other dissolving liquids (such as nail polish remover) should not be used.

This Instructions for Use have been approved by the U.S. Food and Drug Administration.

Distributed by:
Novartis Pharmaceuticals Corporation
East Hanover, New Jersey 07936

© Novartis
December 2018

PRINCIPAL DISPLAY PANEL

NDC 0078-0501-15

Rx only

EXELON® PATCH

(rivastigmine transdermal system)

Each System Delivers 4.6 mg/24 hours

For Transdermal Use Only

Contains 30 Systems

NOVARTIS

PRINCIPAL DISPLAY PANEL

NDC 0078-0502-15

Rx only

EXELON® PATCH

(rivastigmine transdermal system)

Each System Delivers 9.5 mg/24 hours

For Transdermal Use Only

Contains 30 Systems

NOVARTIS

PRINCIPAL DISPLAY PANEL

NDC 0078-0503-15

Rx only

EXELON® PATCH

(rivastigmine transdermal system)

Each System Delivers 13.3 mg/24 hours

For Transdermal Use Only

Contains 30 Systems

NOVARTIS